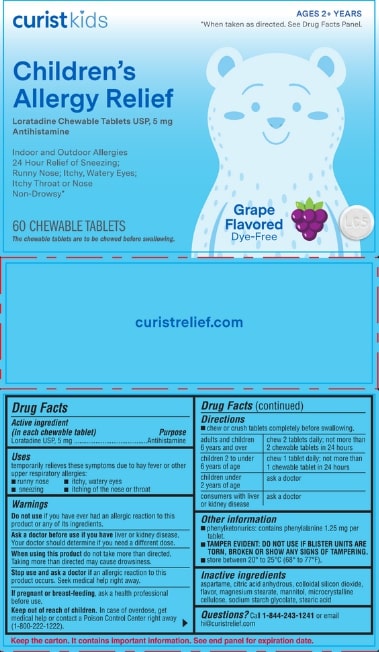 DRUG LABEL: Curist Childrens Allergy Relief
NDC: 72559-031 | Form: TABLET, CHEWABLE
Manufacturer: Little Pharma, Inc.
Category: otc | Type: HUMAN OTC DRUG LABEL
Date: 20240903

ACTIVE INGREDIENTS: LORATADINE 5 mg/1 1
INACTIVE INGREDIENTS: ASPARTAME; MANNITOL; STEARIC ACID; ANHYDROUS CITRIC ACID; MAGNESIUM STEARATE; SODIUM STARCH GLYCOLATE TYPE A POTATO; MICROCRYSTALLINE CELLULOSE; SILICON DIOXIDE

Children's Allergy Relief

Drug Facts

Active ingredient (in each chewable tablet)

Loratadine USP, 5 mg

Purpose

Antihistamine

Uses

temporarily relieves these symptoms due to hay fever or other upper respiratory allergies:

- runny nose
- sneezing
- itchy, watery eyes
- itching of the nose or throat

Warnings

Do not use if you have ever had an allergic reaction to this product or any of its ingredients.

Ask a doctor before use if you have liver or kidney disease. Your doctor should determine if you need a different dose.

When using this product do not take more than directed. Taking more than directed may cause drowsiness.

Stop use and ask a doctor if an allergic reaction to this product occurs. Seek medical help right away.

PREGNANCY OR BREAST FEEDING

If pregnant or breast-feeding, ask a health professional before use.

Keep out of reach of children. In case of overdose, get medical help or contact a Poison Control Center right away (1-800-222-1222).

DOSAGE AND ADMINISTRATION

- chew or crush tablets completely before swallowing.

adults and children 6 years and over | chew 2 tablets daily; not more than 2 chewable tablets in 24 hours
children 2 to under 6 years of age | chew 1 tablet daily; not more than 1 chewable tablets in 24 hours
children under 2 years of age | ask a doctor
consumers with liver or kidney disease | ask a doctor

Other information

- phenylketonurics: contains phenylalanine 1.25 mg per tablet.
- TAMPER EVIDENT: DO NOT USE IF BLISTER UNITS ARE TORN, BROKEN OR SHOW ANY SIGNS OF TAMPERING.
- store between 20º to 25ºC (68º to 77ºF).

Inactive ingredients

aspartame, citric acid anhydrous, colloidal silicon dioxide, flavor, magnesium stearate, mannitol, microcrystalline cellulose, sodium starch glycolate, stearic acid

QUESTIONS

Questions? Call 1-844-243-1241 or email hi@curistrelief.com

Keep the carton. It contains important information. See end panel for expiration date.

REV: 031-43-01

NDC: 72559-031-43

Distributed by: Little Pharma, Inc.

New York, NY 10023

Tableted and Packaged in USA

PACKAGE LABEL

curist kids

Children's Allergy Relief

Loratadine Chewable Tablets USP, 5 mg

Antihistamine

Indoor and Outdoor Allergies

24 Hour Relief of Sneezing;

Runny Nose; Itchy, Watery Eyes;

Itchy Throat or Nose

Non-Drowsy*

60 CHEWABLE TABLETS

The chewable tablets are to be chewed before swallowing.

AGES 2+ YEARS

*When taken as directed. See Drug Facts Panel.

Grape Flavored

Dye-Free

curistrelief.com